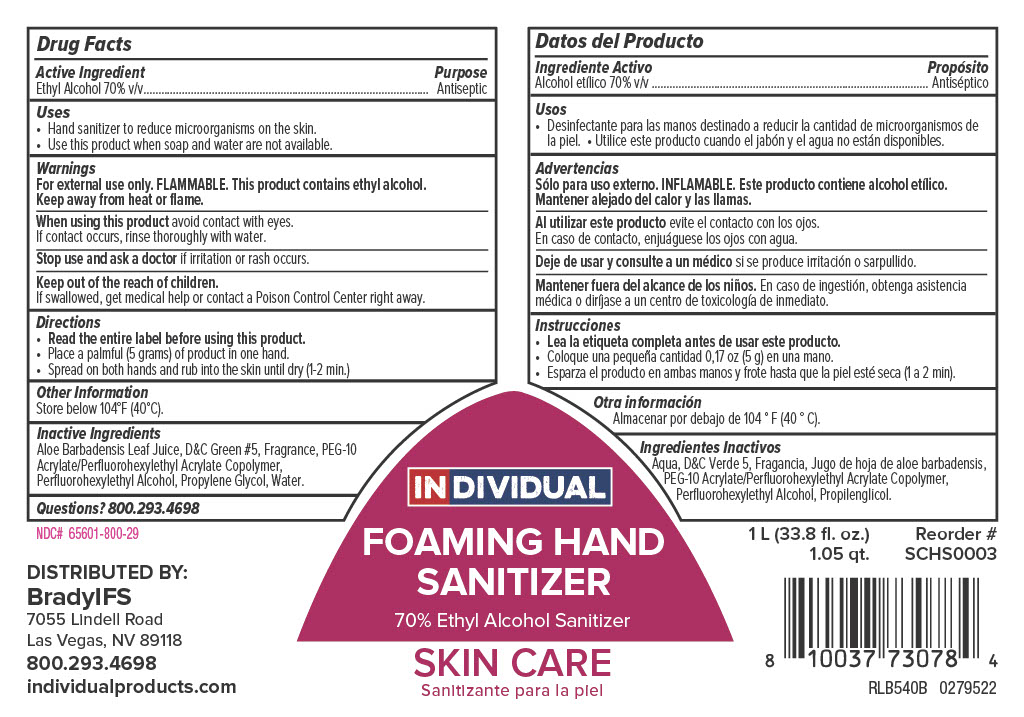 DRUG LABEL: Individual Free and Clear Foaming Antibacterial Skin Cleanser
NDC: 79258-795 | Form: SOAP
Manufacturer: Brady Industries Inc.
Category: otc | Type: HUMAN OTC DRUG LABEL
Date: 20220314

ACTIVE INGREDIENTS: DEHYDRATED ALCOHOL 0.7 mg/1 mL
INACTIVE INGREDIENTS: ALOE VERA LEAF; WATER; PEG-10 ACRYLATE/PERFLUOROHEXYLETHYL ACRYLATE COPOLYMER; D&C GREEN NO. 5; 2-(PERFLUOROHEXYL)ETHANOL; PROPYLENE GLYCOL

Foaming Hand Sanitizer

Active ingredient

Ethyl Alcohol 70% v/v

Uses

Hand sanitizer to reduce microorganisms on the skin.

Use this product when soap and water are not available.

Warnings

For external use only. FLAMMABLE. This product contains ethyl alcohol.

When using this product avoid contact with eyes. If contact occurs, rinse thoroughly with water.

Stop use and ask a doctor if irritation or rash occurs.

Keep out of the reach of children. If swallowed, get medical help or contact a Poison Control Center right away.

Directions

Read entire label before using this product.

Place a palmful (5 grams) of product in one hand.

Spread on both handsand rub into the skin until dry (1-2 min).

Inactive Ingredients

Aloe Barbadensis Leaf Juice, D&C Green #5, Fragrance, PEG-10 Acrylate/Perfluorohexylethyl Acrylate Copolymer, Perfluorohexylethyl Alcohol, Propylene Glycol, Water

Purpose

Antiseptic

Keep out of reach of children

Keep out of the reach of children